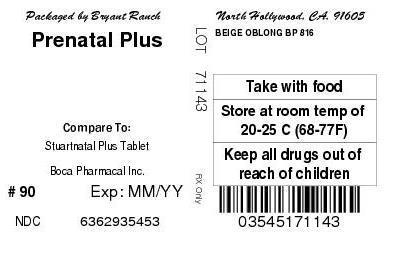 DRUG LABEL: PreNatal Vitamins Plus
NDC: 63629-3545 | Form: TABLET
Manufacturer: Bryant Ranch Prepack
Category: prescription | Type: HUMAN PRESCRIPTION DRUG LABEL
Date: 20140717

ACTIVE INGREDIENTS: VITAMIN A 4000 [iU]/1 1; CHOLECALCIFEROL 400 [iU]/1 1; ZINC 25 mg/1 1; THIAMINE 1.84 mg/1 1; ASCORBIC ACID 120 mg/1 1; CYANOCOBALAMIN 12 ug/1 1; CALCIUM 200 mg/1 1; COPPER 2 mg/1 1; FOLIC ACID 1 mg/1 1; IRON 27 mg/1 1; RIBOFLAVIN 3 mg/1 1; NIACIN 20 mg/1 1; .ALPHA.-TOCOPHEROL ACETATE 22 mg/1 1; PYRIDOXINE 10 mg/1 1
INACTIVE INGREDIENTS: MINERAL OIL; POLYETHYLENE GLYCOLS; ASCORBYL PALMITATE; ANHYDROUS CITRIC ACID; CELLULOSE, MICROCRYSTALLINE; ACACIA; ETHYLCELLULOSES; FD&C BLUE NO. 2; FD&C RED NO. 40; FD&C YELLOW NO. 6; STARCH, CORN; SILICON DIOXIDE; SORBIC ACID; SOY PROTEIN; STEARIC ACID; SUCROSE; TITANIUM DIOXIDE; TRICALCIUM PHOSPHATE; HYPROMELLOSES; MAGNESIUM STEARATE; MALTODEXTRIN; .ALPHA.-TOCOPHEROL, DL-; DEXTROSE; METHYLCELLULOSE (15 CPS); GLYCERYL MONOSTEARATE

Unknown Title

PreNatal Vitamins Plus
Rx Only

DO NOT USE IF IMPRINTED SAFETY SEAL UNDER CAP IS BROKEN OR MISSING

DESCRIPTION

Each Tablet Contains: | Amount per Tablet | % Daily Value
Vitamin A (Acetate and Beta Carotene) | 4000 I.U. | 80%
Vitamin C (Ascorbic Acid) | 120mg. | 200%
Vitamin D-3 (Cholecalciferol) | 400 I.U. | 100%
Vitamin E (dl-Alpha Tocopheryl Acetate) | 22 mg. | 73%
Vitamin B-1 (Thiamine Mononitrate) | 1.84 mg. | 123%
Vitamin B-2 (Riboflavin) | 3 mg. | 176%
Niacin (Niacinamide) | 20 mg | 100%
Vitamin B-6 (Pyridoxine HCl) | 10 mg. | 500%
Folic Acid | 1 mg. | 200%
Vitamin B-12 (Cyanocobalamin) | 12 mcg. | 200%
Calcium (from Calcium Carbonate) | 200 mg. | 20%
Iron (Ferrous Fumarate) | 27 mg. | 150%
Zinc (Zinc Oxide) | 25 mg. | 167%
Copper (Cupric Oxide) | 2 mg. | 100%

Other Ingredients: Ascorbyl Palmitate, Citric Acid anhydrous, DL-alpha Tocopherol, Ethylcellulose, FD&C Blue #2 lake, FD&C Red #40 lake, FD&C Yellow #6 lake, Glucose, Gum Acacia, Hypromellose, Magnesium Stearate, Maize Starch, Maltodextrin, Methylcellulose, Microcrystalline Cellulose, Mineral Oil, Mono- and di-glycerides, Polyethylene Glycol, Pregelatinized Corn Starch, Silicon Dioxide, Sorbic Acid, Soy Protein, Stearic Acid, Sucrose, Titanium Dioxide, Tricalcium Phosphate.

INDICATIONS AND USAGE

Indications: To provide vitamin and mineral supplementation throughout pregnancy and during the postnatal period for both the lactating and nonlactating mother. It is also useful for improving nutritional status prior to conception.

Directions: Before, during and after pregnancy, one tablet daily or as directed by a physician.

CONTRAINDICATIONS

Contraindications: This product is contraindicated in patients with a known hypersensitivity to any of the ingredients.

PRECAUTIONS

Caution: Folic Acid may partially correct the hematological damage due to Vitamin B-12 deficiency of pernicious anemia while the associated neurological damage progresses.

BOXED WARNING

WARNING: Accidental overdose of iron-containing products is a leading cause of fatal poisoning in children under six. Keep this product out of reach of children. In case of accidental overdose, call a physician or Poison Control Center immediately.

WARNINGS

Store at room temperature, USP. Dispense in a well closed light resistant container. KEEP OUT OF THE REACH OF CHILDREN.

REFERENCES

Manufactured for: Boca Pharmacal, Inc., Coral Springs, FL 33065
www.bocapharmacal.com 1-800-354-8460 Iss. 06/12

PACKAGE LABEL

Prenatal Plus